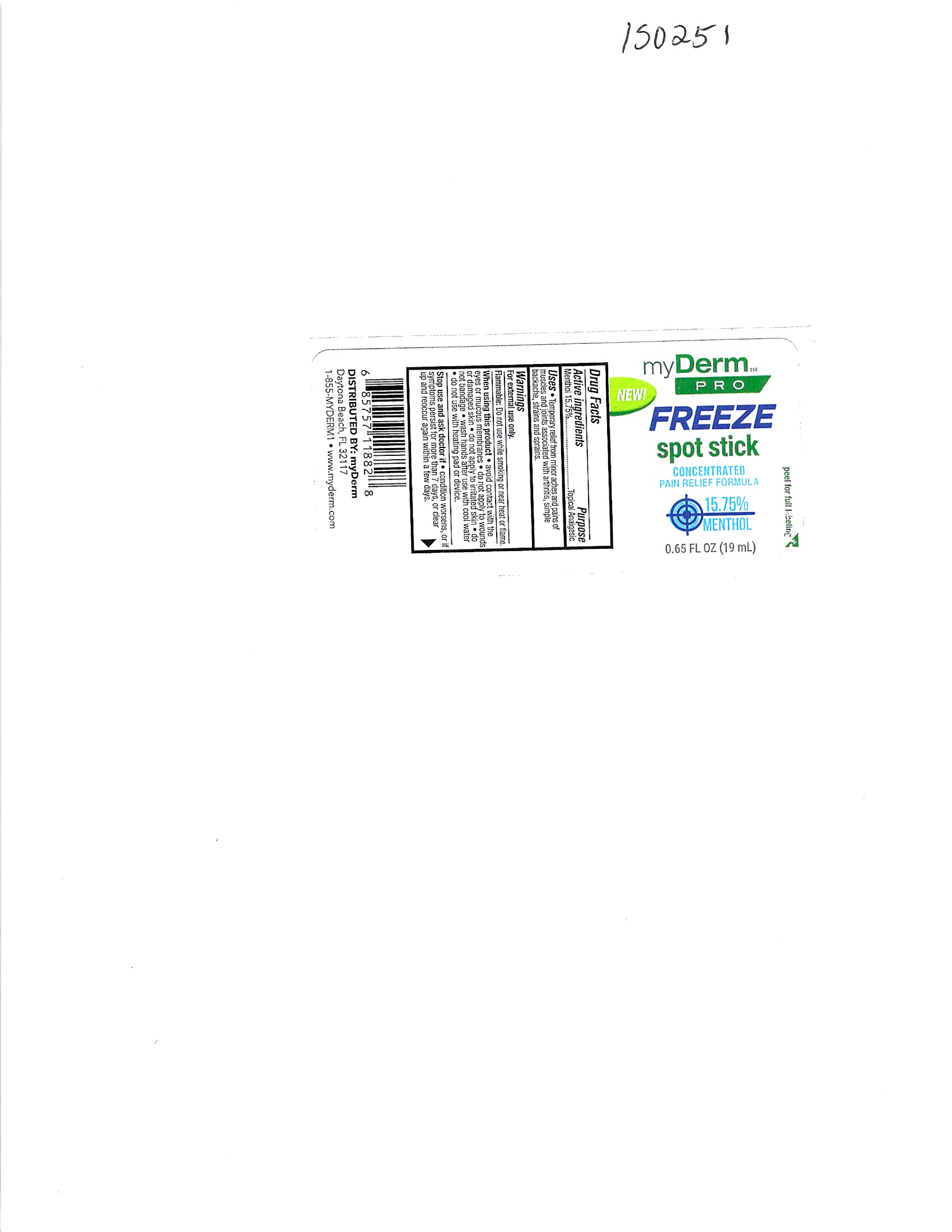 DRUG LABEL: MyDerm Pro Freeze spot stick concentrated pain relief formula 15.75 menthol
NDC: 72667-074 | Form: STICK
Manufacturer: Inspec Solutions
Category: otc | Type: HUMAN OTC DRUG LABEL
Date: 20240624

ACTIVE INGREDIENTS: MENTHOL, (+)- 15.75 g/100 g
INACTIVE INGREDIENTS: ISOPROPYL MYRISTATE; ACETALDEHYDE; ALCOHOL; METHYL ALCOHOL

MyDerm Pro freeze concentrated pain relief formula spot stick 15.75 Menthol

Active Ingredient

Menthol 15.75%

When using this product avoid contact with the eyes or mucous membranes do not apply to wounds or damaged skin do not apply to irritated skin do not bandage wash hands after use with cool water do not use with heating pad or device.

WARNINGS

For external use only.

Stop use and ask doctor if condition worsens, or if symptoms persist for more than 7 days, or clear up and reoccur again within a few days.

PURPOSE

Menthol 15.75%------------------------------------------------Topical Analgesic

Keep out of reach of children. If swallowed, get medical help or contact a Poison Control Center immediately.

DOSAGE AND ADMINISTRATION

Apply to affected area not more than 3 to 4 times a day

INDICATIONS AND USAGE

For external use only

Inactive Ingredients:

Inactive Ingredients:

Purified Water

Ethyl alcohol

ISOPROPYL MYRISTATE

Acetone

Methanol

Acetaldehyde